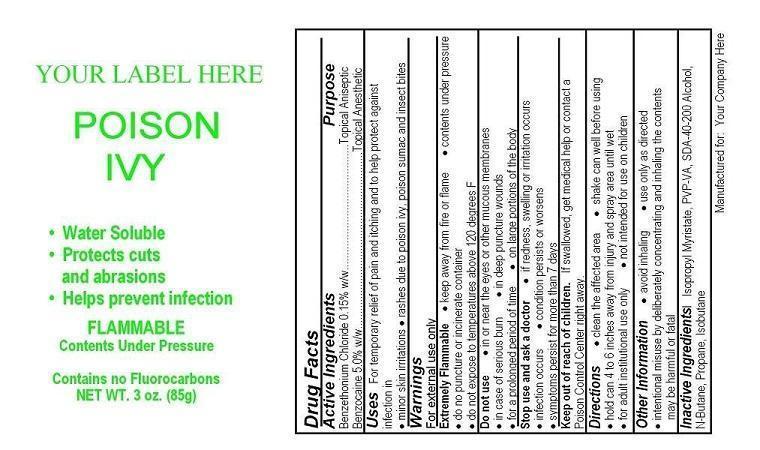 DRUG LABEL: Your Logo Here Poison Ivy First Aid
NDC: 52982-107 | Form: AEROSOL, SPRAY
Manufacturer: Dixon Investments, Inc.
Category: otc | Type: HUMAN OTC DRUG LABEL
Date: 20130409

ACTIVE INGREDIENTS: BENZOCAINE 4250 mg/85 g; BENZETHONIUM CHLORIDE 127.5 mg/85 g
INACTIVE INGREDIENTS: ISOPROPYL MYRISTATE; PVP/VA COPOLYMER; ALCOHOL; BUTANE; PROPANE; ISOBUTANE

YOUR LOGO HERE POISON IVY RELIEF

Active Ingredients

Benzethonium Chloride 0.15% w/w
Benzocaine 5.0% w/w

Purpose

Topical Antiseptic
Topical Anesthetic

Uses

For temporary relief of pain and itching and to help protect against infection in
minor skin irritations
rashes due to poison ivy, poison sumac and insect bites

Warnings

For external use only

Extremely Flammable

keep away from fire or flame
contents under pressure
do not puncture or incinerate container
do not expose to temperatures above 120°F

Do not use

in or near the eyes or other mucous membranes
in case of serious burn
in deep puncture wounds
for a prolonged period of time
on large portions of the body

Stop use and ask a doctor

if redness, swelling or irritation occurs
infection occurs
condition persists or worsens
symptoms persist for more than 7 days

Keep out of reach of children

If swallowed, get medical help or contact a Poison Control Center right away

Directions

clean the affected area
shake can well before using
hold can 4 to 6 inches away from injury and spray area until wet
for adult institutional use only
not intended for children

Other Information

avoid inhaling
use only as directed
intentional misuse by deliberately concentrating and inhaling the contents may be harmful or fatal

Inactive Ingredients

Isopropyl Myristate, PVP-VA, SDA-40-200 Alcohol, N-Butane, Propane, Isobutane